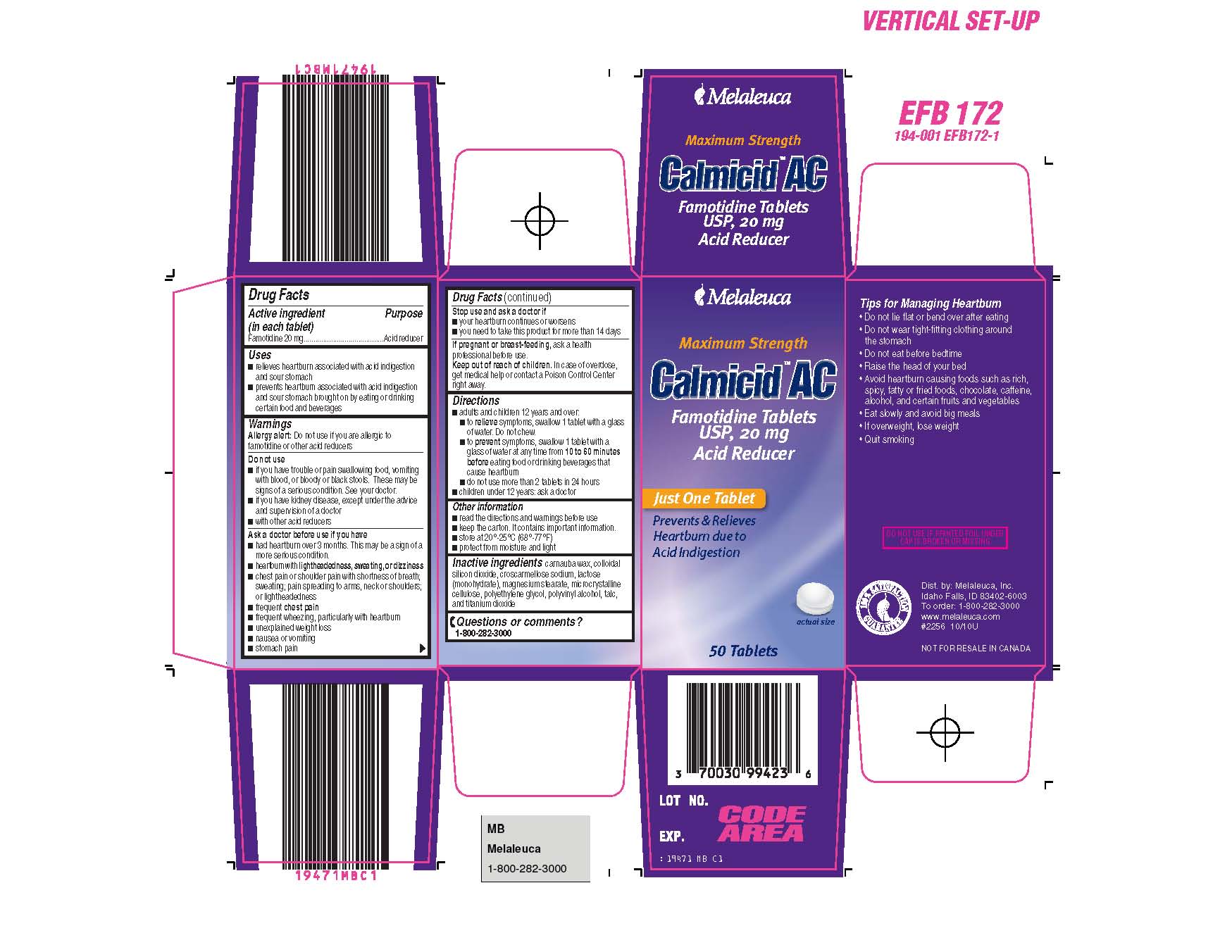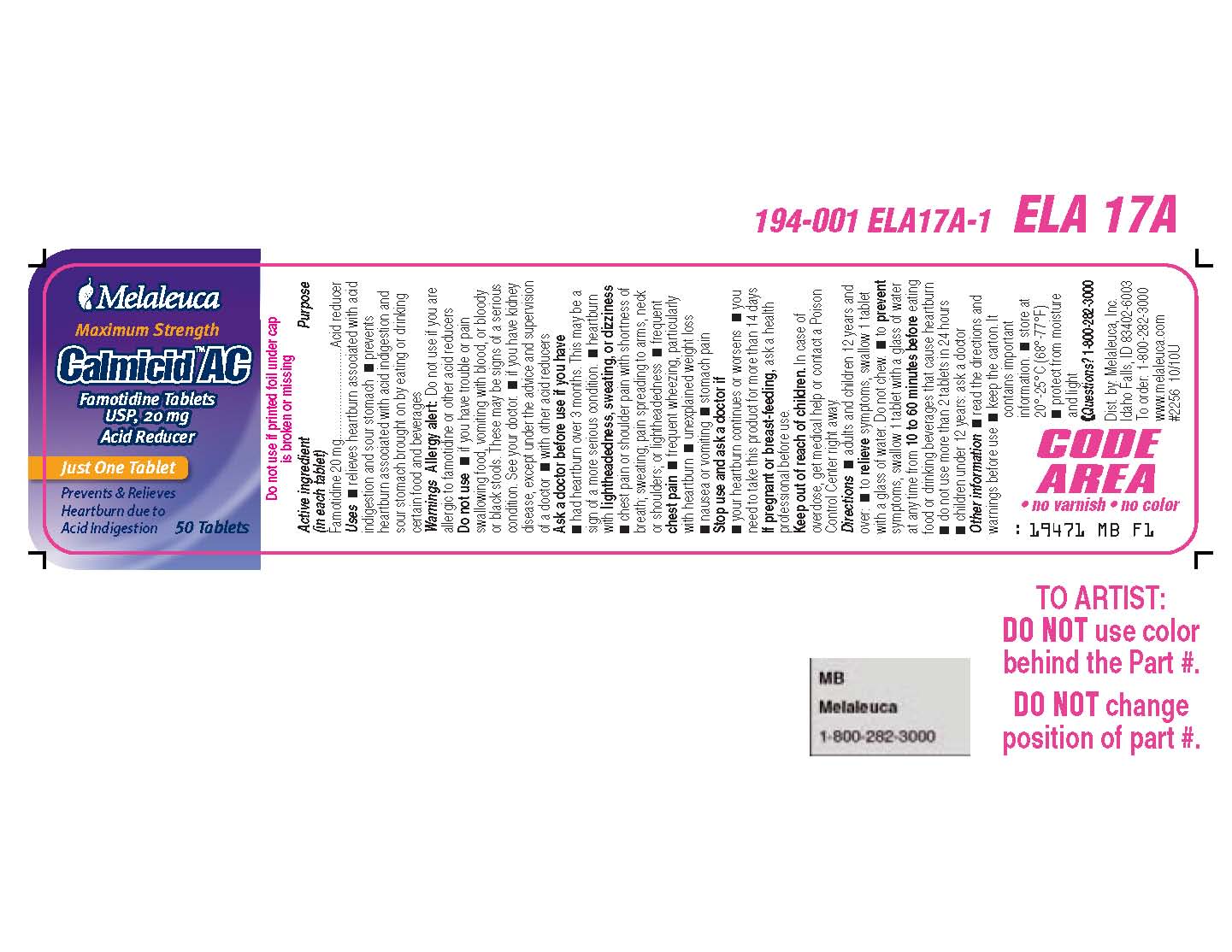 DRUG LABEL: Calmicid AC
NDC: 59368-285 | Form: TABLET, FILM COATED
Manufacturer: Sixarp, LLC
Category: otc | Type: HUMAN OTC DRUG LABEL
Date: 20250918

ACTIVE INGREDIENTS: FAMOTIDINE 20 mg/1 1
INACTIVE INGREDIENTS: CARNAUBA WAX; SILICON DIOXIDE; CROSCARMELLOSE SODIUM; LACTOSE MONOHYDRATE; MAGNESIUM STEARATE; CELLULOSE, MICROCRYSTALLINE; POLYETHYLENE GLYCOL; POLYVINYL ALCOHOL; TALC; TITANIUM DIOXIDE

Calmicid AC Content of Labeling

Purpose
Acid reducer

Use

- relieves heartburn associated with acid indigestion and sour stomach
- prevents heartburn associated with acid indigestion and sour stomach brought on by eating or drinking certain food and beverages

Warnings
Allergy alert:Do not use if you are allergic to famotidine or other acid reducers

Do not use

- if you have trouble or pain swallowing food, vomiting with blood, or bloody or black stools. These may be signs of a serious condition. See your doctor.
- if you have kidney disease, except under the advice and supervision of a doctor
- with other acid reducers

Ask a doctor before use if you have

- had heartburn over three months. This may be a sign of a more serious condition.
- heartburn with lightheadedness, sweating, or dizziness
- chest pain or shoulder pain with shortness of breath; sweating; pain spreading to arms, neck or shoulders; or lightheadedness
- frequent chest pain
- frequent wheezing, particularly with heartburn
- unexplained weight loss
- nausea or vomiting
- stomach pain

Stop use and ask a doctor if

- your heartburn continues or worsens
- you need to take this product for more than 14 days

PREGNANCY OR BREAST FEEDING

If pregnant or breastfeeding,ask a health professional before use.

Keep out of reach of children.In case of overdose, get medical help or contact a Poison Control Center right away.

Directions

- adults and children 12 years and over:

-
  - to relievesymptoms, swallow 1 tablet with a glass of water. Do not chew.
  - to preventsymptoms, swallow 1 tablet with a glass of water at any time from 10 to 60 minutesbeforeeating food or drinking beverages that cause heartburn
  - do not use more than 2 tablets in 24 hours
- children under 12 years: ask a doctor

Active ingredient (in each tablet)

Famotidine 20 mg

Other information

- store at 20°-25°C (68°-77°F)
- protect from moisture and light

INACTIVE INGREDIENT

Inactive ingredientscarnauba wax, colloidal silicon dioxide, croscarmellose sodium, lactose (monohydrrate), magnesium stearate, microcrystalline cellulose, polyethylene glycol, polyvinyl alcohol, talc, and titanium dioxide

Questions or comments?
1-800-282-3000

DO NOT USE IF PRINTED FOIL UNDER CAP IS BROKEN OR MISSING

Other information

- read the directions and warnings before use
- keep the carton, it contains important information.